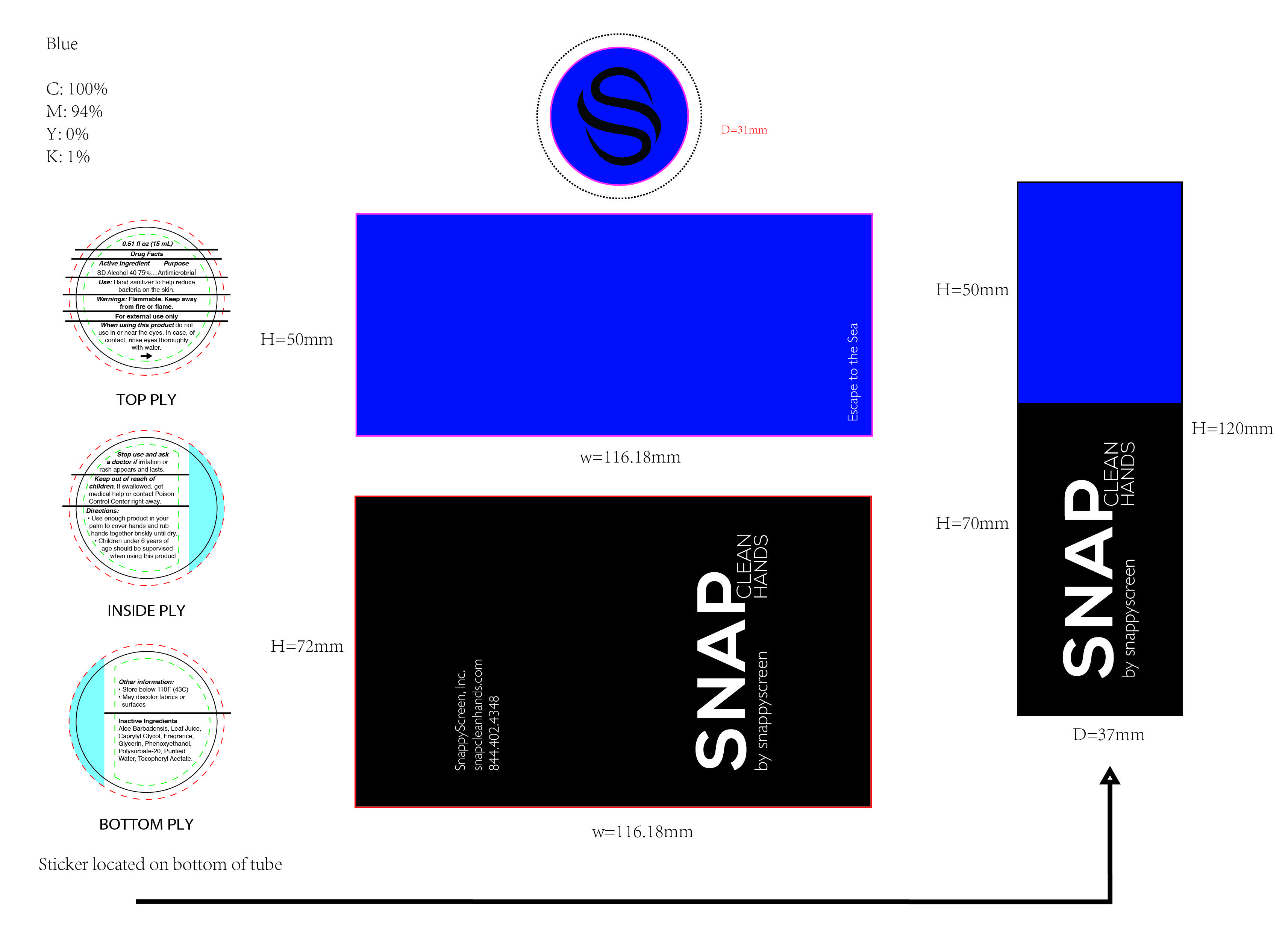 DRUG LABEL: Hand Sanitizer
NDC: 58133-959 | Form: AEROSOL, SPRAY
Manufacturer: Cosmetic Specialty Labs, Inc.
Category: otc | Type: HUMAN OTC DRUG LABEL
Date: 20230503

ACTIVE INGREDIENTS: ALCOHOL 75 mL/100 mL
INACTIVE INGREDIENTS: POLYSORBATE 20; PHENOXYETHANOL; WATER; ALPHA-TOCOPHEROL ACETATE; CAPRYLYL GLYCOL; GLYCERIN; ALOE VERA LEAF

Active Ingredient

SD Alcohol 40 75%

PURPOSE

Antimicrobial

Use

Hand Sanitizer to help reduce bacteria on the skin.

Warnings

Flammable. Keep away from fire or flame. For external use only.

When using this product do not use in or near the eyes. In case of contact, rinse eyes thoroughtly with water.

Stop use and ask a doctor if irritation or rash appears and lasts.

Keep out of reach of children. If swallowed, get medical help or contact a Poison Center right away.

Directions

- Use enough product in your palm to cover hands and rub hands together biskly until dry.
- Children under 6 years of age should be supervised when using this product.

Directions

updated effective date to 05/03/2023

Other information

- Store below 110F (43C)
- May discolor fabrics or surfaces

Inactive ingredients

Aloe Barbadensis Leaf Juice, Caprylyl Glycol, Fragrance, Glycerin, Phenoxyethanol, Polysorbate-20, Purified Water, Tocopheryl Acetate.